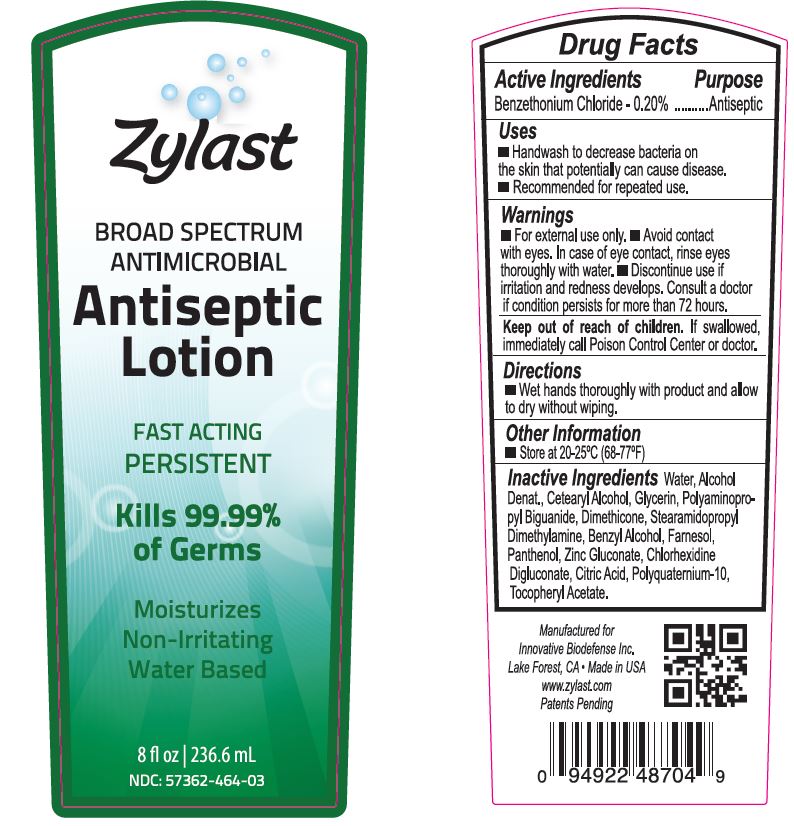 DRUG LABEL: ZylastXP Antiseptic
NDC: 57362-464 | Form: LOTION
Manufacturer: Innovative BioDefense
Category: otc | Type: HUMAN OTC DRUG LABEL
Date: 20210826

ACTIVE INGREDIENTS: BENZETHONIUM CHLORIDE 192.3 mg/1000 mg
INACTIVE INGREDIENTS: WATER

Zylast Antiseptic Lotion 8oz
Drug Facts

ACTIVE INGREDIENT

Benzethonium Chloride - 0.2%

PURPOSE

Antiseptic

ASK DOCTOR

Discontinue use of irritation and redness develops. Consult a doctor if condition persists for more than 72 hours.

DOSAGE AND ADMINISTRATION

Wet hands thoroughly with product and allow to dry without wiping.

WARNINGS

For external use only. Avoid contact with eyes. In case of eye contact, rinse eyes thoroughly with water. Discontinue use if irritation and redness develops. Consult a doctor if condition persists for more than 72 hours. If swallowed, immediately call Poison Control Center or doctor.

INACTIVE INGREDIENT

Water, Alcohol Denat., Cetearyl Alcohol, Glycerin, Polyaminopropyl Biguanide, Dimethicone, Stearamidopropyl Dimethylamine, Benzyl Alcohol, Farnesol, Panthenol, Zinc Gluconate, Chlorhexidine Digluconate, Citric Acid, Polyquaternium-10, Tocopheryl Acetate.

INDICATIONS AND USAGE

Handwash to decrease bacteria on the skin that potentially can cause disease. Recommended for repeated use.

KEEP OUT OF REACH OF CHILDREN

If swallowed, immediately call Poison Control Center or doctor.

PACKAGE LABEL

NDC 57362-464-03

Zylas Antiseptic Lotion 8oz

Broad Spectrum

Antimicrobial

Fast Acting